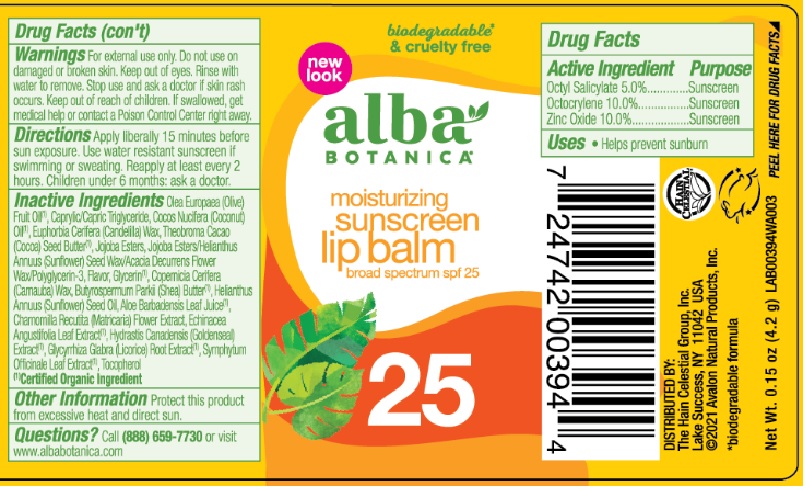 DRUG LABEL: Alba Sunscreen Lip Balm SPF 25
NDC: 61995-3037 | Form: STICK
Manufacturer: The Hain Celestial Group, Inc.
Category: otc | Type: HUMAN OTC DRUG LABEL
Date: 20231206

ACTIVE INGREDIENTS: OCTOCRYLENE 10 g/100 g; ZINC OXIDE 10 g/100 g; OCTISALATE 5 g/100 g
INACTIVE INGREDIENTS: HYDROLYZED JOJOBA ESTERS (POTASSIUM SALTS); ACACIA DECURRENS FLOWER WAX; POLYGLYCERIN-3; ECHINACEA ANGUSTIFOLIA LEAF; ALPHA-TOCOPHEROL ACETATE; ALOE VERA LEAF; HYDROGENATED OLIVE OIL; GLYCERIN; SHEA BUTTER; SUNFLOWER SEED OIL GLYCERETH-8 ESTERS; COCOA BUTTER; GLYCYRRHIZA GLABRA WHOLE; MATRICARIA CHAMOMILLA; SUNFLOWER SEED; HYDRASTIS CANADENSIS WHOLE; CAPRYLIC/CAPRIC/LAURIC TRIGLYCERIDE; COCONUT OIL; SYMPHYTUM OFFICINALE WHOLE; CANDELILLA WAX; CARNAUBA WAX

AL00394-05 Alba Sun Lip Balm SPF 25
14680-1 /B12294

ACTIVE INGREDIENTS

Zinc Oxide 10%

Octocrylene 10%

Octisalate 5%

USES

- Helps prevent sunburns
- Higher SPF gives more sunburn protection

- Apply liberally as needed 15 to 20 minutes before sun exposure

- Reapply as needed or after swimming, perspiring or towel drying

- Children under 6 months of age: ask doctor

WARNINGS

For external use only. When using this product keep out of eyes. Rinse with water to remove. Stop use and ask a doctor if rash or irritation develops and lasts. Keep out of reach of children. If swallowed, get medical help or contact Poison Center right away.

QUESTIONS?

Call (888) 659-7730 or visit www.AlbaBotanica.com

Made in the U.S.A.

INACTIVE INGREDIENT

Olea Europaea (Olive) Fruit Oil (1), Caprylic/Capric Triglyceride, Cocos Nucifera (Coconut) Oil (1), Euphorbia Cerifera (Candelilla) Wax, Theobroma Cacao (Cocoa) Seed Butter (1), Jojoba Esters, Jojoba Esters/Helianthus Annuus (Sunflower) Seed Wax/Acacia Decurrens Flower Wax/Polyglycerin-3, Flavor, Glycerin (1), Copernicia Cerifera (Carnauba) Wax, Butyrospermum Parkii (Shea) Butter (1), Helianthus Annuus (Sunflower) Seed Oil, Aloe Barbadensis Leaf Juice (1), Chamomilla Recutita (Matricaria) Flower Extract, Echinacea Angustifolia Leaf Extract (1), Hydrastis Canadensis (Goldenseal) Root Extract (1), Glycyrrhiza Glabra (Licorice) Root Extract (1), Symphytum Officinale Leaf Extract (1), Tocopherol

(1)Certified Organic Ingredient

DOSAGE AND ADMINISTRATION

Sunscreen Lip Balm

Keep out of reach of children

PURPOSE

Sunscreen